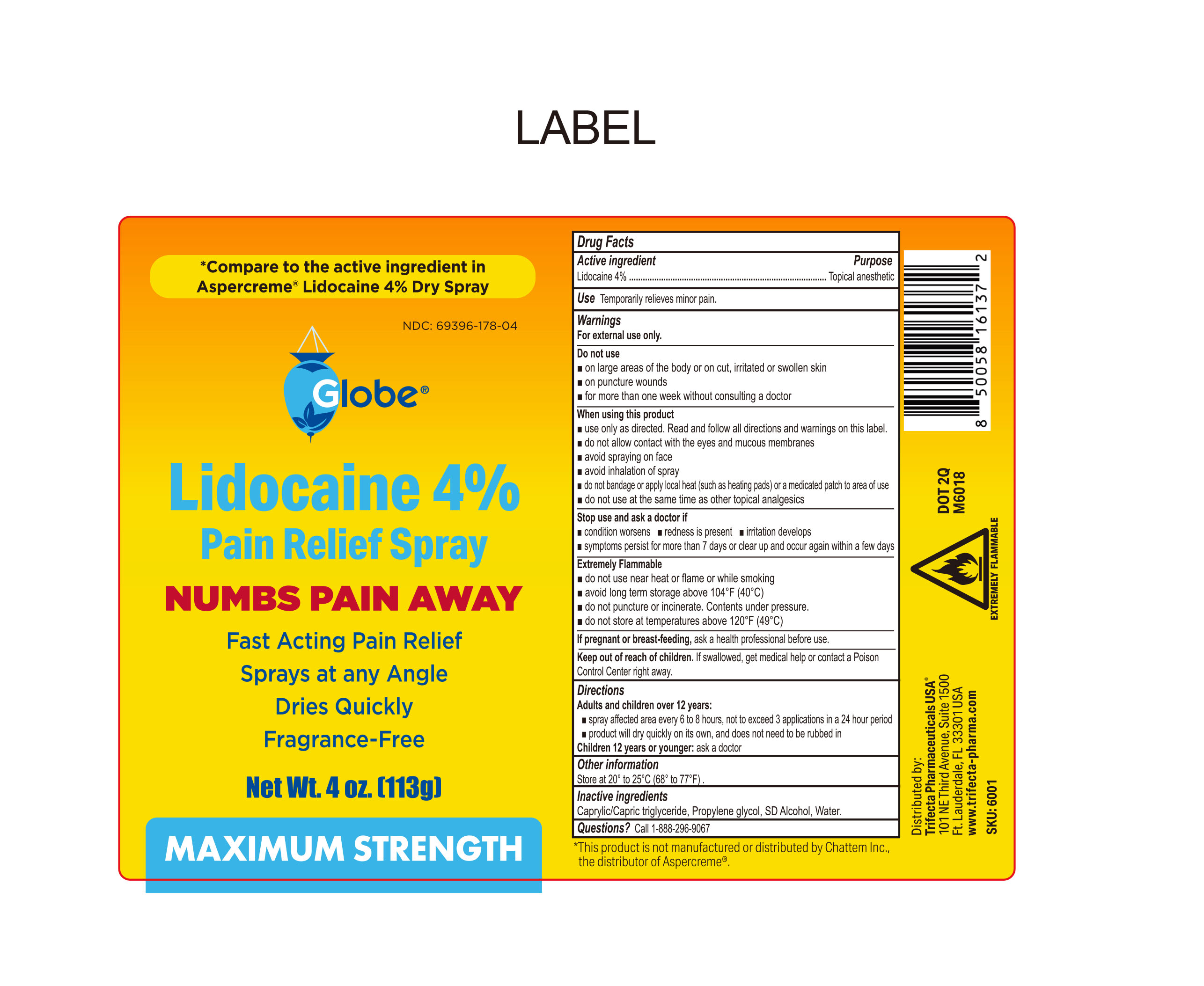 DRUG LABEL: Lidocaine Pain Relief
NDC: 69396-178 | Form: SPRAY
Manufacturer: Trifecta Pharmaceuticals USA, LLC.
Category: otc | Type: HUMAN OTC DRUG LABEL
Date: 20260126

ACTIVE INGREDIENTS: LIDOCAINE 4 g/100 g
INACTIVE INGREDIENTS: ALCOHOL; CAPRYLIC/CAPRIC TRIGLYCERIDE; PROPYLENE GLYCOL; WATER

Globe Lidocaine 4% Pain Relief Spray

Active Ingredient

Lidocaine 4%

Purpose

Topical Anesthetic

Warnings

For External Use Only

Extemely Flammable

- do not use near heat or flame or while smoking
- avoid long term storage above 104ºF (40ºC)
- do not puncture or incinerate. Contents under pressure
- do not store at temerature above 120ºF (49ºC).

Uses

Temporarily relieves minor pain

When Using this product

- Use only as directed. Read and follow all directions and warnings on this label.
- do not allow contact with the eyes and mucous membranes
- avoid spraying on face
- avoid inhalation of spray
- do not bandage or apply local heat such as heating pads or a medeicated patch to area of use
- do not sue at thesame timea s other topical analgesics.

Ask doctor before use if you have

- Deep or puncture wounds
- Animal Bites
- Serious burns

Do not use

- on large areas of the body or on cut, irritated or swollen skin
- on puncture wounds
- for more than one week without consulting doctor

Stop use and ask a doctor

- If condition worsens
- redness is present
- irritation develops
- sysmptoms persist for more than 7 days or clear up and occur again within a few days

Keep out of the reach of children

If swallowed, get medical help or contact a Poison Control Center right away

Pregnant or Breast Feeding

ask a health professional before use.

Directions

Adults and children over 12 years

- Spray affected area every 6 to 8 hours, not to exceed 3 applications i n a 24 hour period.
- Product will dry quickly on its own and does not need to be rubbed in

Children 12 years or younger: ask a doctor

Other information

- Store at controlled room temperature 68º-77ºF (20º-25ºC)

Inactive Ingredients

Caprylic Capric triglyceride, propylene glycol, SD alcohol, Water

Questions or Comments

Call 1-888-296-9067

Distributed By:

Trifecta Pharmaceuticals USA, LLC.

101 NE Third Avenue, Suite 1500

Ft. Lauderdale, FL. 33301 USA

www.trifecta-pharma.com

SKU: 6001

* This product is not manufactured or distributed by Chattem Inc. the distributor of Aspercreme®.